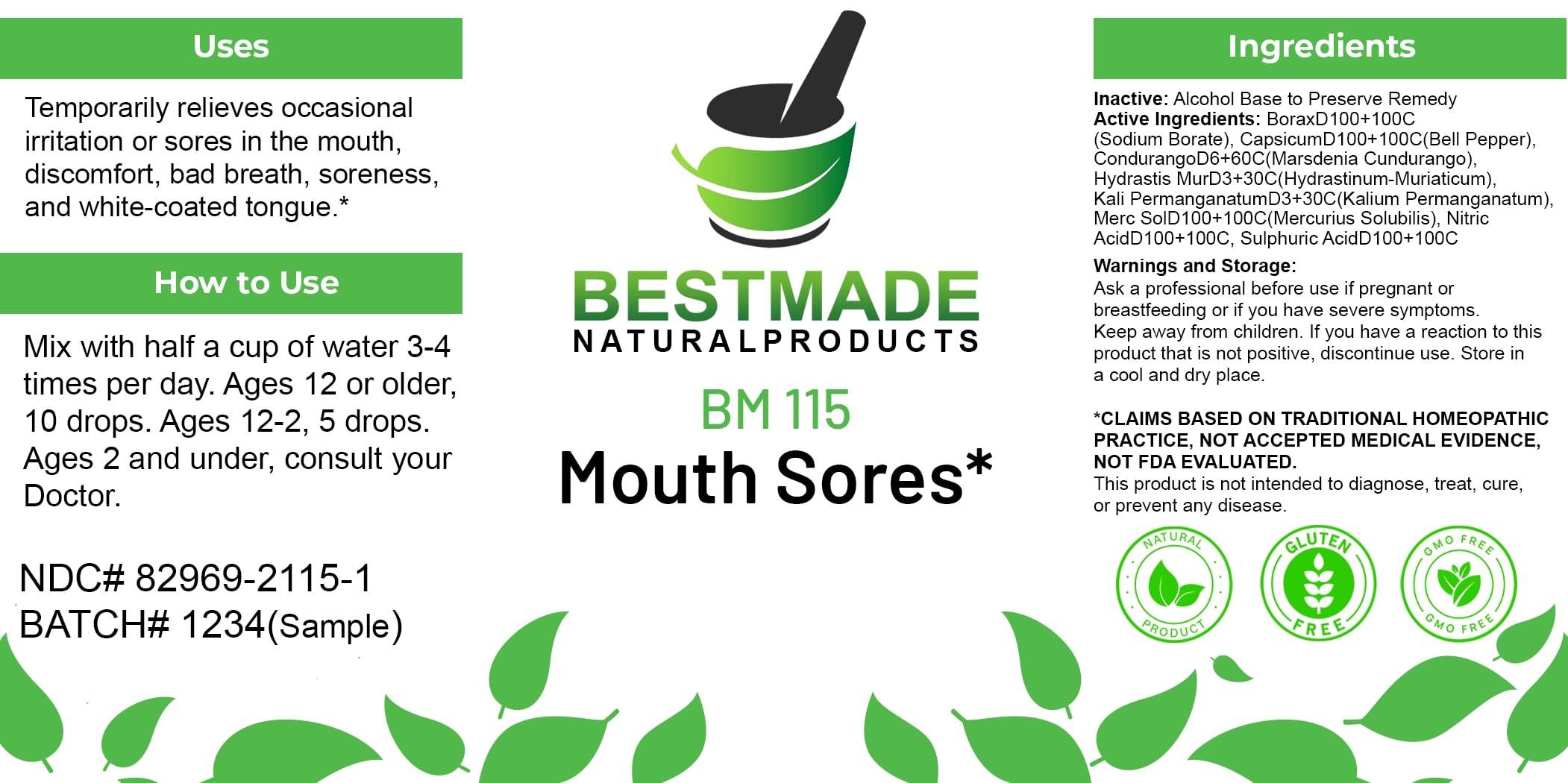 DRUG LABEL: Bestmade Natural Products BM115
NDC: 82969-2115 | Form: LIQUID
Manufacturer: Bestmade Natural Products
Category: homeopathic | Type: HUMAN OTC DRUG LABEL
Date: 20250207

ACTIVE INGREDIENTS: SODIUM BORATE 30 [hp_C]/30 [hp_C]; NITRIC ACID 30 [hp_C]/30 [hp_C]; MERCURIUS SOLUBILIS 30 [hp_C]/30 [hp_C]; HYDRASTININE HYDROCHLORIDE 30 [hp_C]/30 [hp_C]; RUEHSSIA CUNDURANGO BARK 30 [hp_C]/30 [hp_C]; CAPSICUM 30 [hp_C]/30 [hp_C]; SULFURIC ACID 30 [hp_C]/30 [hp_C]; POTASSIUM PERMANGANATE 30 [hp_C]/30 [hp_C]
INACTIVE INGREDIENTS: ALCOHOL 30 [hp_C]/30 [hp_C]

BM115

DOSAGE AND ADMINISTRATION

How to Use

Mix with half a cup of water 3-4 times per day. Ages 12 or older, 10 drops. Ages 12-2, 5 drops. Ages 2 and under, consult your Doctor.

INACTIVE INGREDIENT

Ingredients

Inactive: Alcohol Base to Preserve Remedy

ACTIVE INGREDIENT

Active Ingredients: BoraxD100+100C (Sodium Borate), CapsicumD100+100C(Bell Pepper), CondurangoD6+60C(Marsdenia Condurango), Hydrastis MuD3+30C(Hydrastinum-Muriaticum), Kali PermanganatumD3+30C (Kalium Permanganatum), Merc SoliD100+100C(Mercurius Solubilis), Nitric AcidD100+100C, Sulphuric AcidD100+100C

Uses

Temporarily relieves occasional irritation or sores in the mouth, discomfort, bad breath, soreness, and white-coated tongue.*

*CLAIMS BASED ON TRADITIONAL HOMEOPATHIC PRACTICE, NOT ACCEPTED MEDICAL EVIDENCE. NOT FDA EVALUATED.

This product is not intended to diagnose, treat, cure, or prevent any disease.

Uses

Temporarily relieves occasional irritation or sores in the mouth, discomfort, bad breath, soreness, and white-coated tongue.*

*CLAIMS BASED ON TRADITIONAL HOMEOPATHIC PRACTICE, NOT ACCEPTED MEDICAL EVIDENCE. NOT FDA EVALUATED.

This product is not intended to diagnose, treat, cure, or prevent any disease.

Warnings and Storage:

Ask a professional before use if pregnant or breastfeeding or if you have severe symptoms. Keep away from children. If you have a reaction to this product that is not positive, discontinue use. Store in a cool and dry place.

*CLAIMS BASED ON TRADITIONAL HOMEOPATHIC PRACTICE, NOT ACCEPTED MEDICAL EVIDENCE. NOT FDA EVALUATED.

This product is not intended to diagnose, treat, cure, or prevent any disease.

KEEP OUT OF REACH OF CHILDREN

Warnings and Storage:

Ask a professional before use if pregnant or breastfeeding or if you have severe symptoms. Keep away from children. If you have a reaction to this product that is not positive, discontinue use. Store in a cool and dry place.

Entire package label